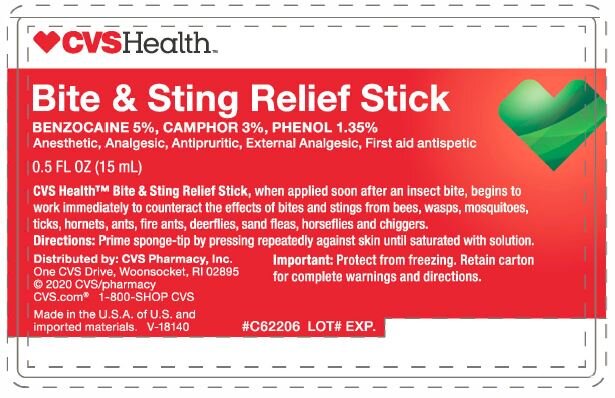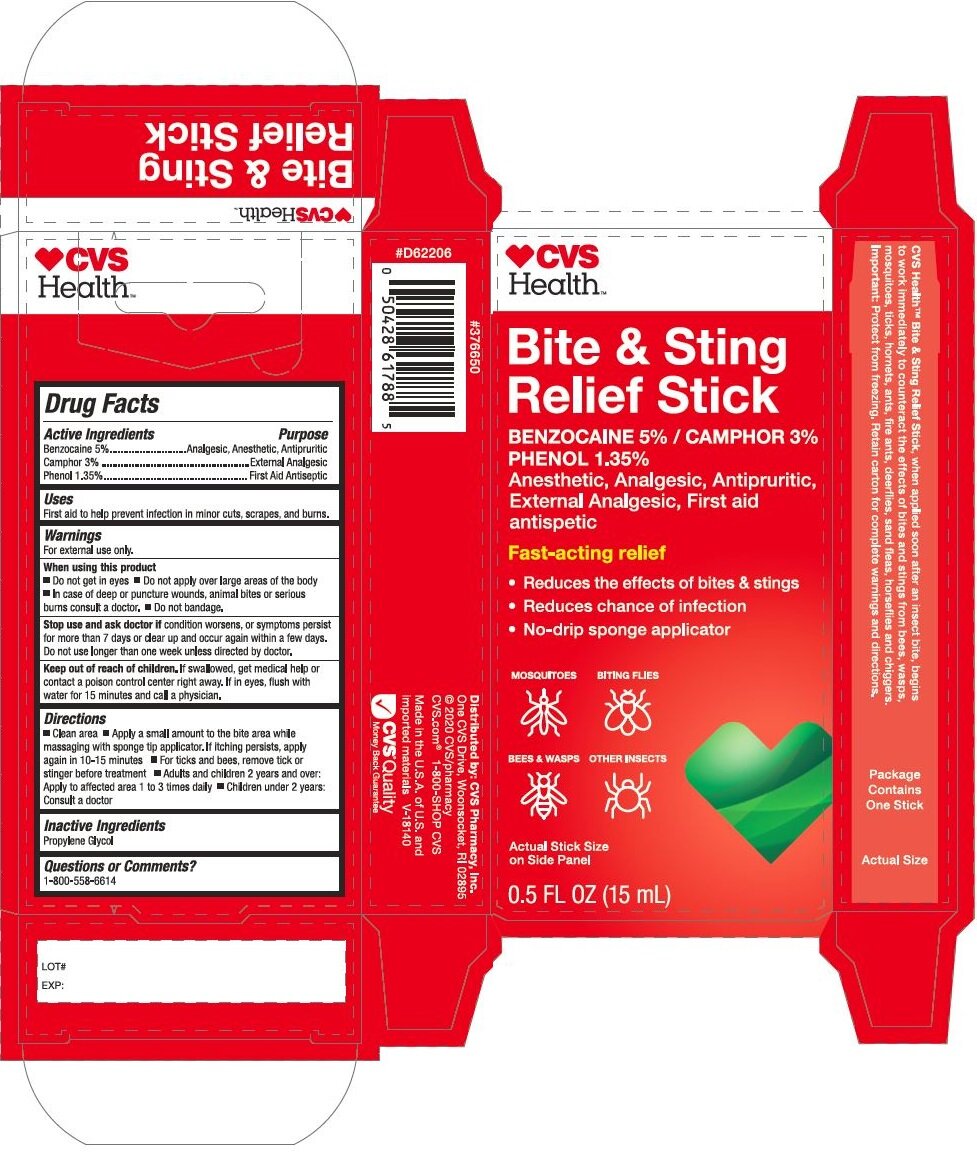 DRUG LABEL: Bite and Sting Relief Stick
NDC: 69842-731 | Form: LIQUID
Manufacturer: CVS Health
Category: otc | Type: HUMAN OTC DRUG LABEL
Date: 20220113

ACTIVE INGREDIENTS: BENZOCAINE 0.05 g/1 g; CAMPHOR (SYNTHETIC) 0.03 g/1 g; PHENOL 0.0135 g/1 g
INACTIVE INGREDIENTS: PROPYLENE GLYCOL

CVS Bite and Sting Relief Stick

PURPOSE

First aid to help prevent infection in minor cuts, scrapes, and bums.

Drug Facts

Active ingredients

Active ingredients | Pupose
Benzocaine 5% | Analgesic, Anesthetic, Antipuritic
Camphor 3.0% | First Aid Antiseptic
Phenol 1.35% | External Analgesic

Uses

First aid to help prevent infection in minor cuts, scrapes, and bums.

Warnings

For external use only.

When using this product
■ Do not get in eyes ■ Do not apply over large areas of the body
■ In case of deep or puncture wounds, animal bites or serious
burns consult a doctor. ■ Do not bandage.

Stop use and ask doctor if condition worsens, or symptoms persist for more than 7 days or clear up and occur again within a few days. Do not use longer than one week unless directed by doctor.

Keep out of reach of children. If swallowed, get medical help or contact a poison control center right away. If in eyes, flush with
water for 15 minutes and call a physician.

Directions

■ Clean area ■ Apply a small amount to the bite area while massaging with sponge tip applicator. If itching persists, apply again in 10-15 minutes ■ For ticks and bees, remove tick or stinger before treatment ■ Adults and children 2 years and over: Apply to affected area 1 to 3 times daily ■ Children under 2 years: Consult a doctor

Inactive ingredients

Propylene Glycol

Questions or Comments?

1-800-558-6614

Principal Display Panel - 15 mL Stick Carton

CVS

HEALTH

Bite & Sting

Relief Stick

Benzocaine 5% / Phenol 1.35%

Camphor 3.0%

Anesthetic, Analgesic, Antipuritic,

External Analgesic, First Aid

antiseptic

Fast-acting relief

Reduces the effects of bites & stings
Reduces chance of infections
No-drip sponge applicator

MOSQUITOES BITING FLIES

BEES & WASPS OTHER INSECTS

Actual Stick Size

On Side Panel

0.5 FL. OZ. (15 mL)